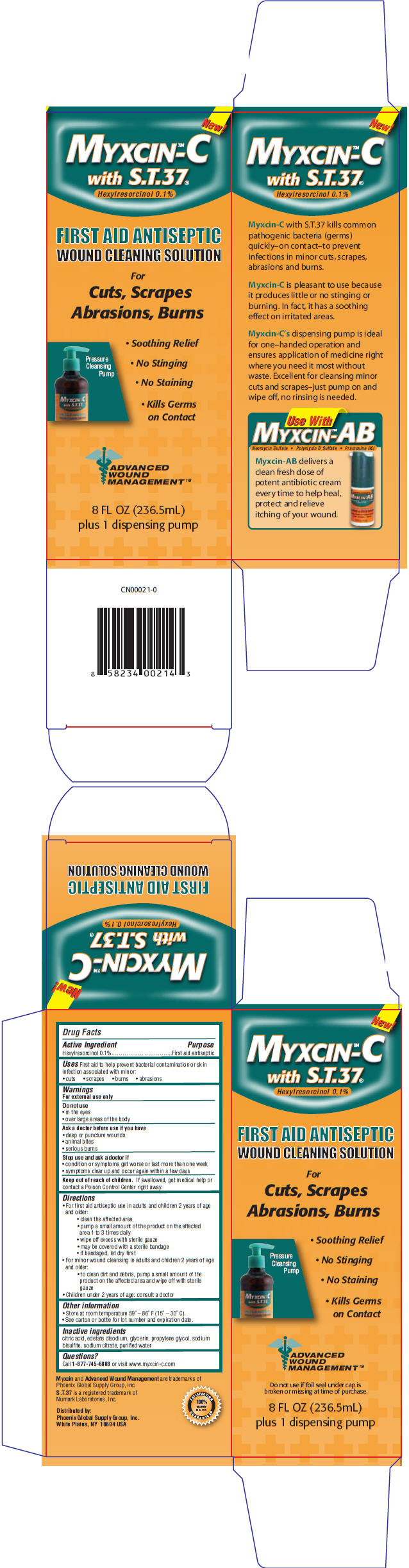 DRUG LABEL: Myxcin-C
NDC: 52426-520 | Form: SOLUTION
Manufacturer: Phoenix Global Supply Group, Inc.
Category: otc | Type: HUMAN OTC DRUG LABEL
Date: 20120214

ACTIVE INGREDIENTS: Hexylresorcinol 1.1 mg/1 mL
INACTIVE INGREDIENTS: CITRIC ACID MONOHYDRATE; EDETATE DISODIUM; GLYCERIN; PROPYLENE GLYCOL; SODIUM BISULFITE; SODIUM CITRATE; WATER

Myxcin™-C

Drug Facts

Active Ingredient

Hexylresorcinol 0.1%

Purpose

First aid antiseptic

Uses

First aid to help prevent bacterial contamination or skin infection associated with minor:

- cuts
- scrapes
- burns
- abrasions

Warnings

For external use only

Do not use

- in the eyes
- over large areas of the body

Ask a doctor before use if you have

- deep or puncture wounds
- animal bites
- serious burns

Stop use and ask a doctor if

- condition or symptoms get worse or last more than one week
- symptoms clear up and occur again within a few days

Keep out of reach of children. If swallowed, get medical help or contact a Poison Control Center right away.

Directions

- For first aid antiseptic use in adults and children 2 years of age and older:
  - clean the affected area
  - pump a small amount of the product on the affected area 1 to 3 times daily
  - wipe off excess with sterile gauze
  - may be covered with a sterile bandage
  - if bandaged, let dry first
- For minor wound cleansing in adults and children 2 years of age and older:
  - to clean dirt and debris, pump a small amount of the product on the affected area and wipe off with sterile gauze
- Children under 2 years of age: consult a doctor

Other information

- Store at room temperature 59° – 86° F (15° – 30° C).
- See carton or bottle for lot number and expiration date.

Inactive ingredients

citric acid, edetate disodium, glycerin, propylene glycol, sodium bisulfite, sodium citrate, purified water

Questions?

Call 1-877-745-6888 or visit www.myxcin-c.com

Distributed by:
Phoenix Global Supply Group, Inc.
White Plains, NY 10604 USA

PRINCIPAL DISPLAY PANEL - 236.5 mL Bottle Carton

New!

MYXCIN™-C
with S.T.37®

Hexylresorcinol 0.1%

FIRST AID ANTISEPTIC
WOUND CLEANING SOLUTION

For
Cuts, Scrapes
Abrasions, Burns

Pressure
Cleansing
Pump

- Soothing Relief
- No Stinging
- No Staining
- Kills Germs
  on Contact

ADVANCED
WOUND
MANAGEMENT ™

8 FL OZ (236.5mL)
plus 1 dispensing pump